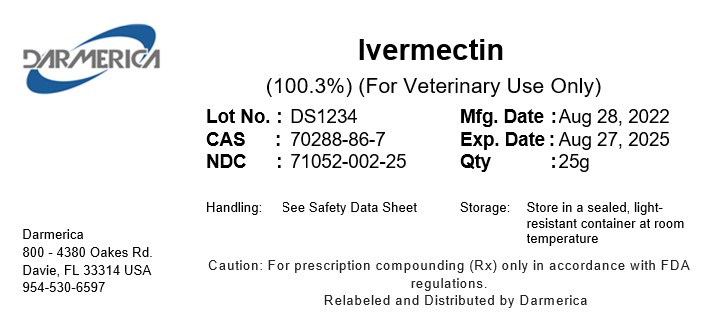 DRUG LABEL: Ivermectin
NDC: 71052-002 | Form: POWDER
Manufacturer: DARMERICA, LLC
Category: other | Type: BULK INGREDIENT - ANIMAL DRUG
Date: 20251024

ACTIVE INGREDIENTS: IVERMECTIN 1 g/1 g

Ivermectin